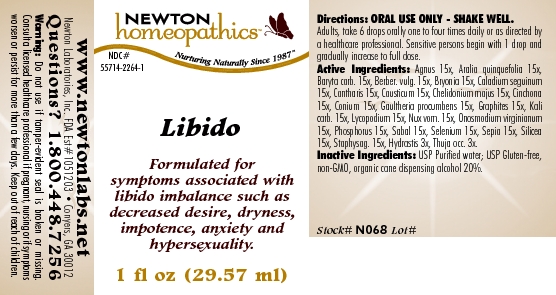 DRUG LABEL: Libido 
NDC: 55714-2264 | Form: LIQUID
Manufacturer: Newton Laboratories, Inc.
Category: homeopathic | Type: HUMAN OTC DRUG LABEL
Date: 20110301

ACTIVE INGREDIENTS: Chaste Tree 15 [hp_X]/1 mL; American Ginseng 15 [hp_X]/1 mL; Barium Carbonate 15 [hp_X]/1 mL; Berberis Vulgaris Root Bark 15 [hp_X]/1 mL; Bryonia Alba Root 15 [hp_X]/1 mL; Dieffenbachia Seguine 15 [hp_X]/1 mL; Lytta Vesicatoria 15 [hp_X]/1 mL; Causticum 15 [hp_X]/1 mL; Chelidonium Majus 15 [hp_X]/1 mL; Cinchona Officinalis Bark 15 [hp_X]/1 mL; Conium Maculatum Flowering Top 15 [hp_X]/1 mL; Gaultheria Procumbens Top 15 [hp_X]/1 mL; Graphite 15 [hp_X]/1 mL; Potassium Carbonate 15 [hp_X]/1 mL; Lycopodium Clavatum Spore 15 [hp_X]/1 mL; Strychnos Nux-vomica Seed 15 [hp_X]/1 mL; Onosmodium Virginianum Whole 15 [hp_X]/1 mL; Phosphorus 15 [hp_X]/1 mL; Saw Palmetto 15 [hp_X]/1 mL; Selenium 15 [hp_X]/1 mL; Sepia Officinalis Juice 15 [hp_X]/1 mL; Silicon Dioxide 15 [hp_X]/1 mL; Delphinium Staphisagria Seed 15 [hp_X]/1 mL; Goldenseal 3 [hp_X]/1 mL; Thuja Occidentalis Leafy Twig 3 [hp_X]/1 mL
INACTIVE INGREDIENTS: Alcohol

Libido

INDICATIONS & USAGE SECTION

Libido Formulated for symptoms associated with libido imbalance such as decreased desire, dryness, impotence, anxiety and hypersexuality.

DOSAGE & ADMINISTRATION SECTION

Directions: ORAL USE ONLY - SHAKE WELL. Adults, take 6 drops orally one to four times daily or as directed by a healthcare professional. Sensitive persons begin with 1 drop and gradually increase to full dose.

OTC - ACTIVE INGREDIENT SECTION

Agnus 15x, Aralia quinquefolia 15x, Baryta carb. 15x, Berber. vulg. 15x, Bryonia 15x, Caladium seguinum 15x, Cantharis 15x, Causticum 15x, Chelidonium majus 15x, Cinchona 15x, Conium 15x, Gaultheria procumbens 15x, Graphites 15x, Kali carb. 15x, Lycopodium 15x, Nux vom. 15x, Onosmodium virginianum 15x, Phosphorus 15x, Sabal 15x, Selenium 15x, Sepia 15x, Silicea 15x, Staphysag. 15x, Hydrastis 3x, Thuja occ. 3x.

OTC - PURPOSE SECTION

Formulated for symptoms associated with libido imbalance such as decreased desire, dryness, impotence, anxiety and hypersexuality.

INACTIVE INGREDIENT SECTION

Inactive Ingredients: USP Purified Water; USP Gluten-free, non-GMO, organic cane dispensing alcohol 20%.

QUESTIONS SECTION

www.newtonlabs.net Newton Laboratories, Inc. FDA Est # 1051203 - Conyers, GA 30012
Questions? 1.800.448.7256

WARNINGS SECTION

Warning: Do not use if tamper - evident seal is broken or missing. Consult a licensed healthcare professional if pregnant, nursing or if symptoms worsen or persist for more than a few days. Keep out of reach of children.

OTC - PREGNANCY OR BREAST FEEDING SECTION

Consult a licensed healthcare professional if pregnant, nursing or if symptoms worsen or persist for more than a few days.

OTC - KEEP OUT OF REACH OF CHILDREN SECTION

Keep out of reach of children.